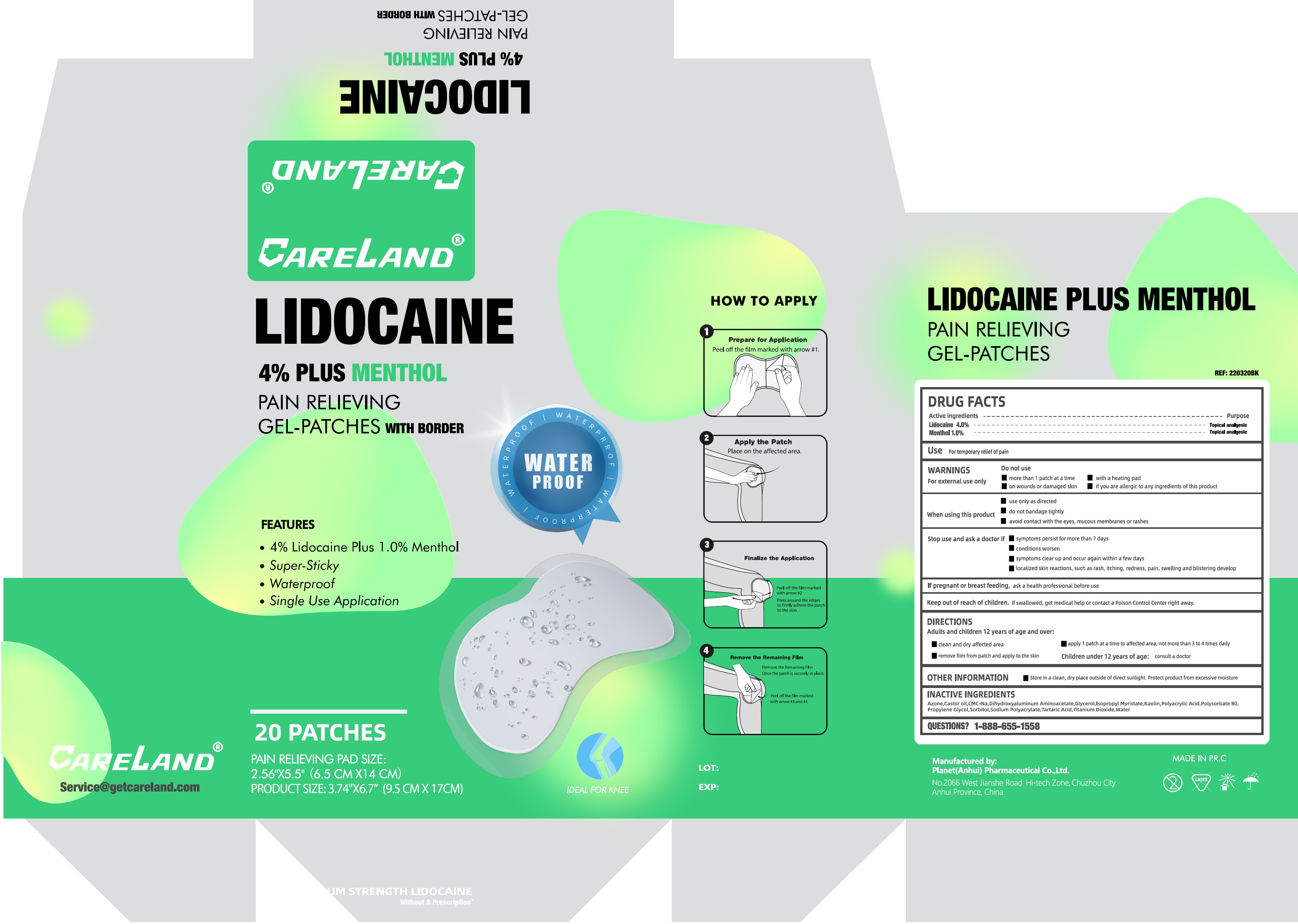 DRUG LABEL: Careland Lidocaine 4 plus menthol pain relieving gel-patches with border for knee
NDC: 75568-013 | Form: PATCH
Manufacturer: Planet (Anhui) Pharmaceutical Co., Ltd.
Category: otc | Type: HUMAN OTC DRUG LABEL
Date: 20260212

ACTIVE INGREDIENTS: LIDOCAINE 40 mg/1 g; MENTHOL 10 mg/1 g
INACTIVE INGREDIENTS: CASTOR OIL; DIHYDROXYALUMINUM AMINOACETATE; GLYCERIN; ISOPROPYL MYRISTATE; KAOLIN; POLYSORBATE 80; PROPYLENE GLYCOL; SORBITOL; TARTARIC ACID; TITANIUM DIOXIDE; WATER; LAUROCAPRAM

Careland Lidocaine 4% plus menthol pain relieving gel-patches with border for knee

Active ingredients

Lidocaine 4.0%

Menthol 1.0%

Purpose

Topical analgesic

Use

For temporary relief of pain

WARNINGS

For external use only

Do not use

- more than 1 patch at a time
- on wounds or damaged skin
- with a heating pad
- if you are allergic to any ingredients of this product

When using this product

- use only as directed
- do not bandage tightly
- avoid contact with the eyes, mucous membranes, or rashes

Stop use and ask a doctor if

- symptoms persist for more than 7 days
- conditions worsen
- symptoms clear up and occur again within a few days
- localized skin reactions, such as rash, itching, redness, pain, swelling and blistering develop

If pregnant or breast-feeding,

ask a health professional before use

Keep out of reach of children.

If swallowed, get medical help or contact a Poison Control Center right away.

DIRECTIONS

Adults and children 12 years of age and over:

- clean and dry affected area
- remove film from patch and apply to the skin
- apply 1 patch at a time to affected area, not more than 3 to 4 times daily

Children under 12 years of age:consult a doctor

OTHER INFORMATION

- Store in a clean, dry place outside of direct sunlight. Protect product from excessive moisture

INACTIVE INGREDIENTS

Azone,Castor oil,CMC-Na,Dihydroxyaluminum Aminoacetate,Glycerol,Isopropyl Myristate, Kaolin,Ployacrylic Acid,Polysorbate 80,Propylene Glycol,Sorbitol,Sodium Polyacrylate, Tartaric Acid, Titanium Dioxide,Water

QUESTIONS?

1-888-655-1558